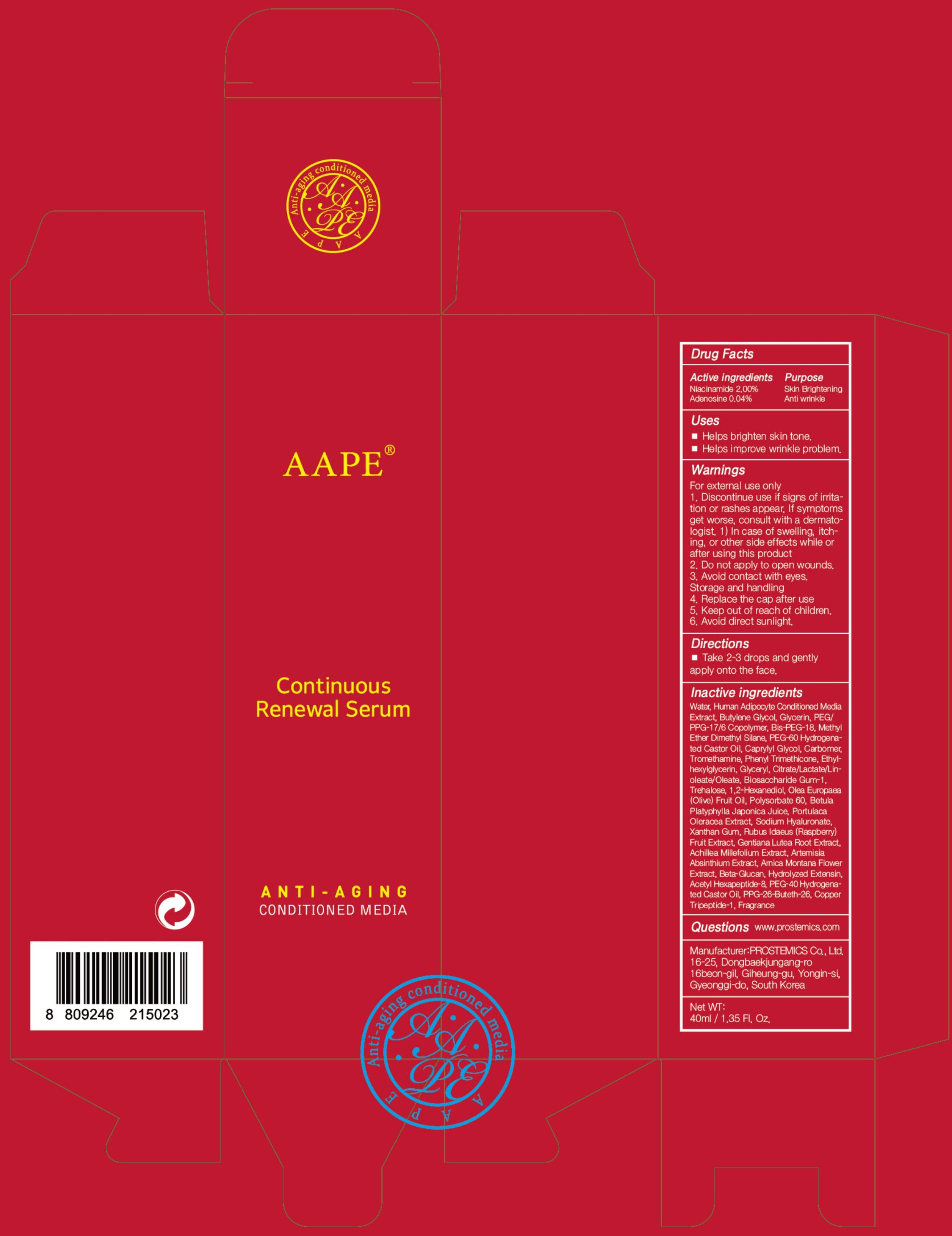 DRUG LABEL: AAPE Continuous Renewal Serum
NDC: 62041-210 | Form: LIQUID
Manufacturer: PROSTEMICS Co., Ltd.
Category: otc | Type: HUMAN OTC DRUG LABEL
Date: 20190826

ACTIVE INGREDIENTS: Niacinamide 0.80 g/40 mL; Adenosine 0.01 g/40 mL
INACTIVE INGREDIENTS: Water; Butylene Glycol

ACTIVE INGREDIENT

Active ingredients: Niacinamide 2.00%, Adenosine 0.04%

INACTIVE INGREDIENT

Inactive ingredients:
Water, Human Adipocyte Conditioned Media Extract, Butylene Glycol, Glycerin, PEG/PPG-17/6 Copolymer, Bis-PEG-18, Methyl Ether Dimethyl Silane, PEG-60 Hydrogenated Castor Oil, Caprylyl Glycol, Carbomer, Tromethamine, Phenyl Trimethicone, Ethylhexylglycerin, Glyceryl, Citrate/Lactate/Linoleate/Oleate, Biosaccharide Gum-1, Trehalose, 1,2-Hexanediol, Olea Europaea (Olive) Fruit Oil, Polysorbate 60, Betula Platyphylla, Japonica Juice, Portulaca Oleracea Extract, Sodium Hyaluronate, Xanthan Gum, Rubus Idaeus (Raspberry) Fruit Extract, Gentiana Lutea Root Extract, Achillea Millefolium Extract, Artemisia Absinthium Extract, Arnica Montana Flower Extract, Beta-Glucan, Hydrolyzed Extensin, Acetyl Hexapeptide-8, PEG-40 Hydrogenated, Castor Oil, PPG-26-Buteth-26, Copper Tripeptide-1

PURPOSE

Purpose: Skin Brightening, Anti wrinkle

WARNINGS

For external use only
1. Discontinue use if signs of irritation or rashes appear. If symptoms get worse, consult with a dermatologist. 1) In case of swelling, itching, or other side effects while or after using this product
2. Do not apply to open wounds.
3. Avoid contact with eyes.
Storage and handling
4. Replace the cap after use
5. Keep out of reach of children.
6. Avoid direct sunlight.

KEEP OUT OF REACH OF CHILDREN

Uses

Helps brighten skin tone.

Helps improve wrinkle problem.

Directions

Take 2-3 drops and gently apply onto the face.